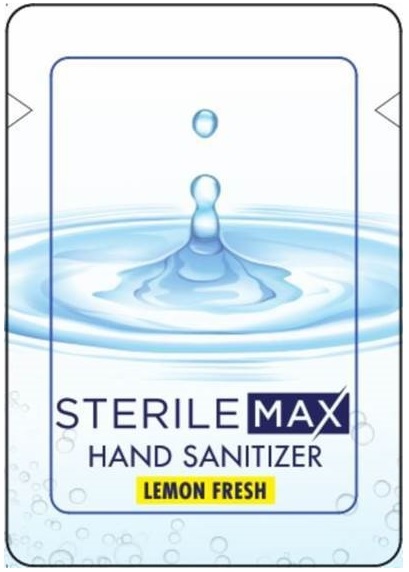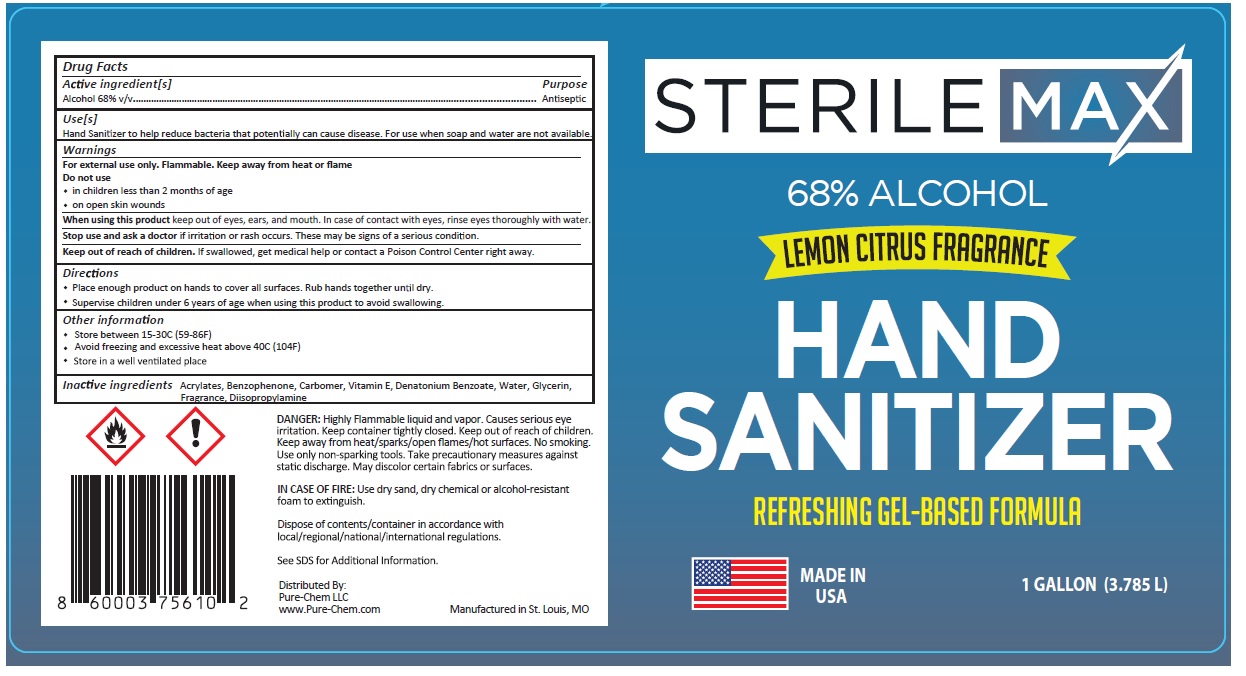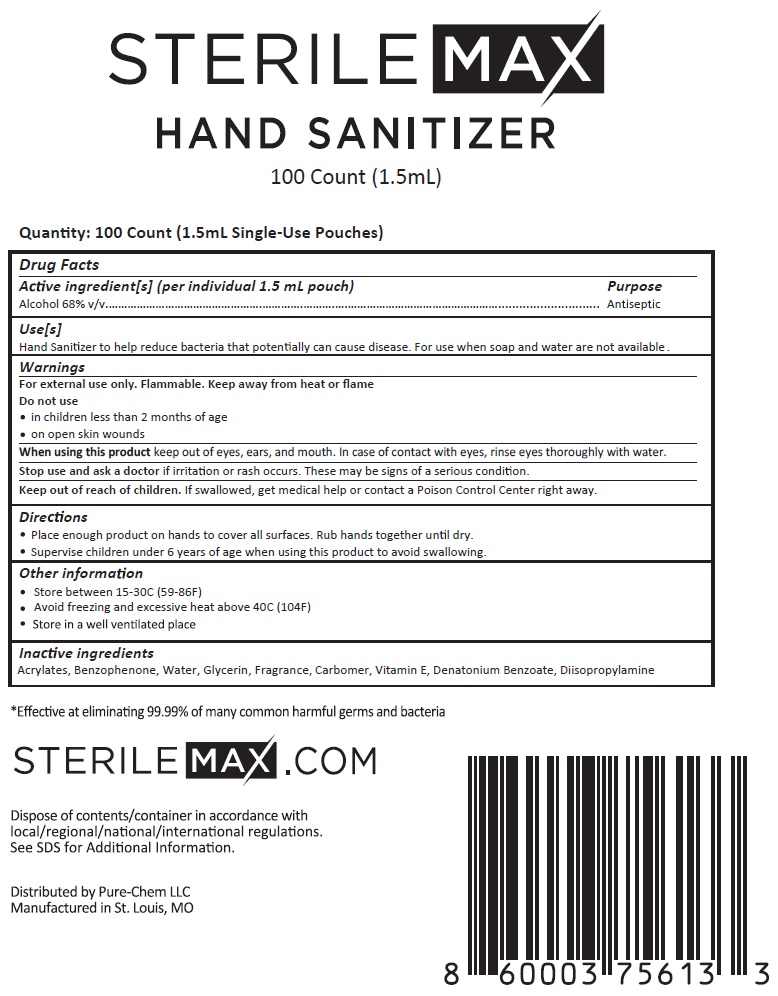 DRUG LABEL: SterileMAX HAND SANITIZER
NDC: 79325-862 | Form: GEL
Manufacturer: Pure-chem, Llc
Category: otc | Type: HUMAN OTC DRUG LABEL
Date: 20201022

ACTIVE INGREDIENTS: ALCOHOL 68 mL/100 mL
INACTIVE INGREDIENTS: BUTYL ACRYLATE/METHYL METHACRYLATE/METHACRYLIC ACID COPOLYMER (18000 MW); BENZOPHENONE; CARBOMER HOMOPOLYMER, UNSPECIFIED TYPE; .ALPHA.-TOCOPHEROL; DENATONIUM BENZOATE; WATER; GLYCERIN; DIISOPROPYLAMINE

STERILEMAX HAND SANITIZER

Active ingredient[s]

Alcohol 68% v/v

Purpose

Antiseptic

Use[s]

Hand Sanitizer to help reduce bacteria that potentially can cause disease. For use when soap and water are not available.

Warnings

For external use only. Flammable. Keep away from heat or flame

Do not use

• in children less than 2 months of age

• on open skin wounds

When using this product keep out of eyes, ears, and mouth. In case of contact with eyes, rinse eyes thoroughly with water.

Stop use and ask a doctor if irritation or rash occurs. These may be signs of a serious condition.

Keep out of reach of children. If swallowed, get medical help or contact a Poison Control Center right away.

Directions

• Place enough product on hands to cover all surfaces. Rub hands together until dry.

• Supervise children under 6 years of age when using this product to avoid swallowing.

Other information

• Store between 15-30C (59-86F)

• Avoid freezing and excessive heat above 40C (104F)

• Store in a well ventilated place

Inactive ingredients

Acrylates, Benzophenone, Carbomer, Vitamin E, Denatonium Benzoate, Water, Glycerin, Fragrance, Diisopropylamine

LEMON CITRUS FRAGRANCE

REFRESHING GEL-BASED FORMULA

MADE IN USA

DANGER: Highly Flammable liquid and vapor. Causes serious eye irritation. Keep container tightly closed. Keep out of reach of children. Keep away from heat/sparks/open flames/hot surfaces. No smoking. Use only non-sparking tools. Take precautionary measures against static discharge. May discolor certain fabrics or surfaces.

IN CASE OF FIRE: Use dry sand, dry chemical or alcohol-resistant foam to extinguish.

Dispose of contents/container in accordance with local/regional/national/international regulations.

See SDS for Additional Information.

Distributed By:

Pure-Chem LLC

www.Pure-Chem.com

Manufactured in St. Louis, MO